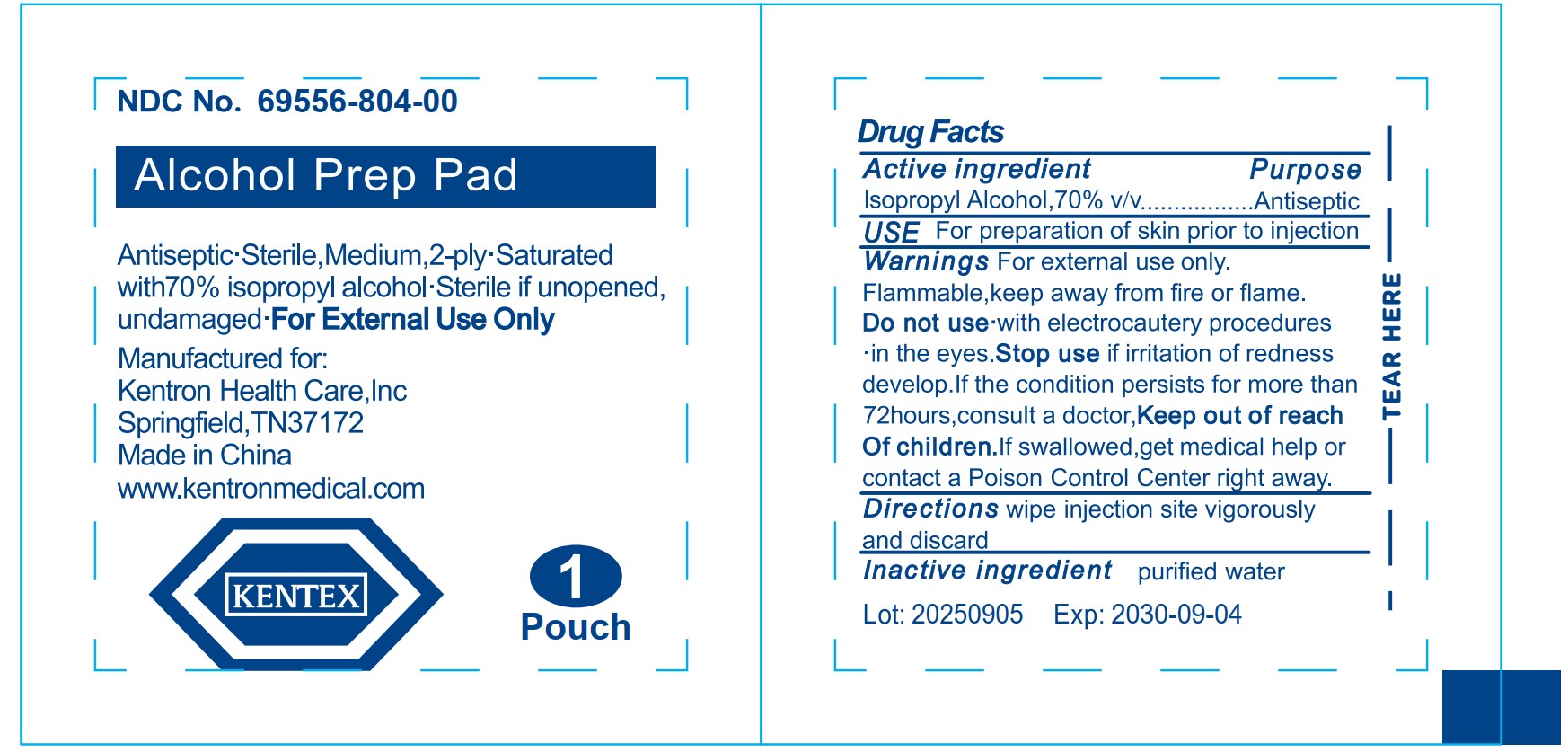 DRUG LABEL: Kentex Alcohol Prep Pad Saturated with Isopropyl Alcohol
NDC: 69556-804 | Form: LIQUID
Manufacturer: Kentron Healthcare, Inc.
Category: otc | Type: HUMAN OTC DRUG LABEL
Date: 20251010

ACTIVE INGREDIENTS: ISOPROPYL ALCOHOL 70 mL/100 mL
INACTIVE INGREDIENTS: WATER

Kentex Alcohol Prep Pad Saturated with 70% Isopropyl Alcohol

Active ingredient

Isopropyl Alcohol,70% v/v

Purpose

Antiseptic

USE

For preparation of skin prior to injection

Warnings

For external use only.
Flammable,keep away from fire or flame.

Do not use

• with electrocautery procedures
• in the eyes.

Stop use if

irritation of redness develop. If the condition persists for more than 72 hours, consuIt a doctor,

Keep out of reach Of children.

lf swallowed, get medical help or contact a Poison Control Center right away.

Directions

wipe injection site vigorously and discard

Inactive ingredient

purified water